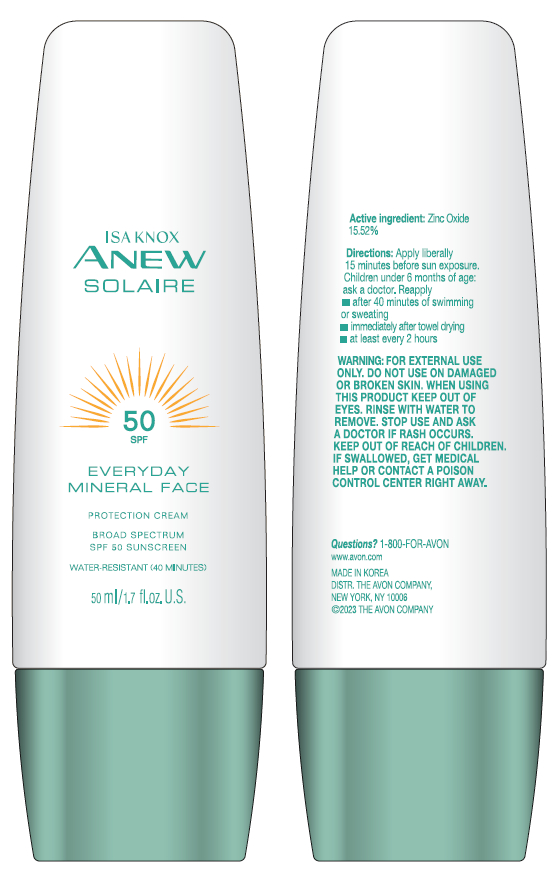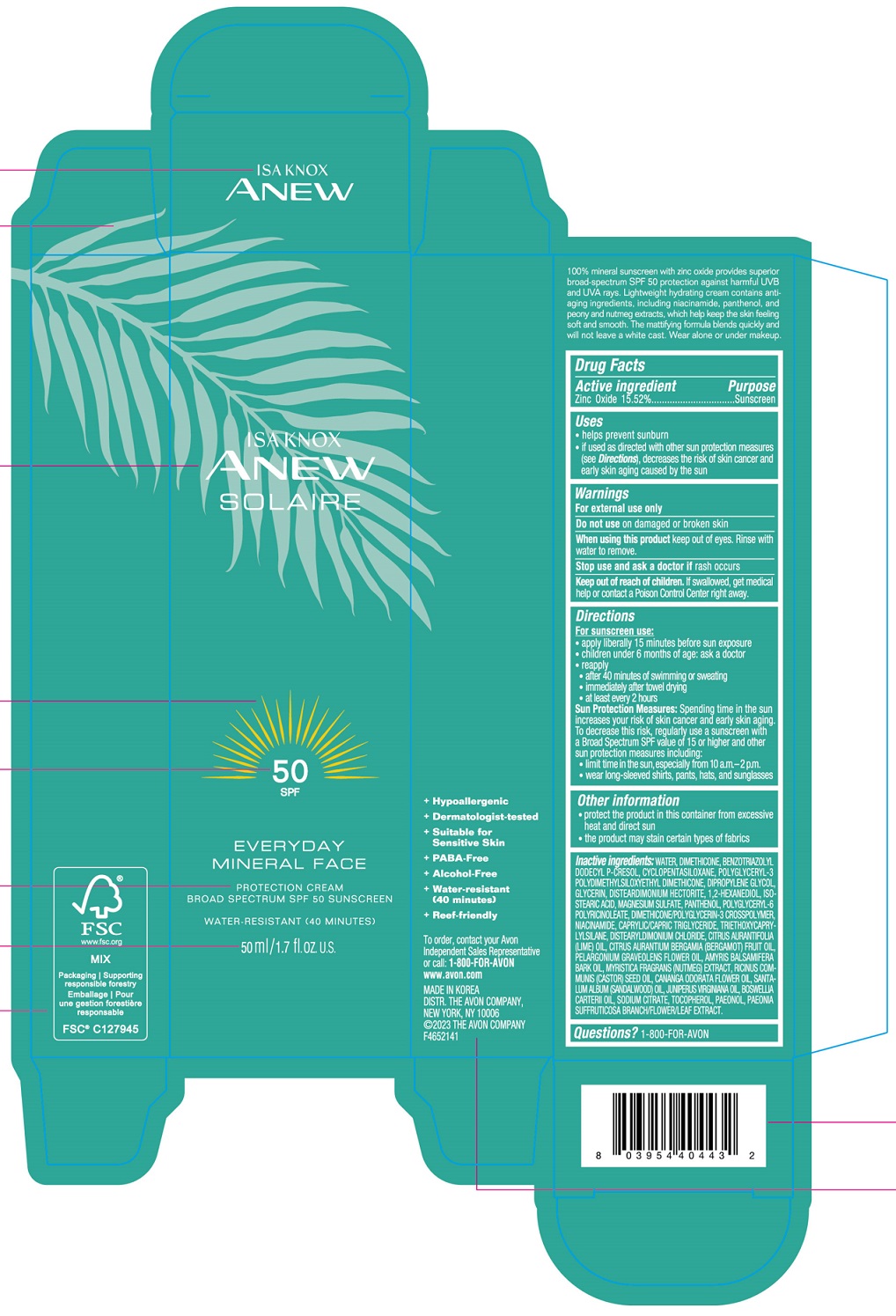 DRUG LABEL: ISA KNOX ANEW SOLAIRE EVERYDAY MINERAL FACE PROTECTION BROAD SPECTRUM SPF 50 SUNSCREEN
NDC: 72330-511 | Form: CREAM
Manufacturer: fmg Co.Ltd
Category: otc | Type: HUMAN OTC DRUG LABEL
Date: 20250101

ACTIVE INGREDIENTS: ZINC OXIDE 15.52 g/50 mL
INACTIVE INGREDIENTS: WATER

72330-511-01 Isa Knox Anew Solaire Everyday Mineral Face Protection Cream Broad Spectrum SPF 50 Sunscreen

ACTIVE INGREDIENTS

Zinc Oxide 15.52%

PURPOSE

SUNSCREEN

USES

- helps prevent sunburn
- if used as directed with other sun protection measures (see Directions), decreases the risk of skin cancer and early skin aging caused by the sun

WARNINGS

For external use only

- Do not useon damaged or broken skin

WHEN USING

- When using this productkeep out of eyes. Rinse with water to remove.

- Stop use and ask a doctor ifrash occurs

- Keep out of reach of children.If swallowed, get medical help or contact a Poison Control Center right away.

DIRECTIONS

For sunscreen use:

- apply liberally 15 minutes before sun exposure
- children under 6 months of age: ask a doctor
- reapply
- - after 40 minutes of swimming or sweating
- - immediately after towel drying
- - at least every 2 hours

Sun Protection Measures:Spending time in the sun increases your risk of skin cancer and early skin aging. To decrease this risk, regularly use a sunscreen with a Broad Spectrum SPF value of 15 or higher and other sun protection measures including:

- limit time in the sun, especially from 10 a.m.-2 p.m.
- wear long-sleeved shirts, pants, hats, and sunglasses

OTHER INFORMATION

- protect the product in this container from excessive heat and direct sun
- the product may stain certain types of fabrics

INACTIVE INGREDIENTS

WATER

QUESTIONS?

1-800-FOR-AVON

+ Hypoallergenic

+ Dermatologist-tested

+ Suitable for Sensitive Skin
+ PABA-Free
+ Alcohol-Free
+ Water-resistant (40 minutes)
+ Reef-friendly

To order, contact your Avon
Indenpendent Sales Representative
or call: 1-800-FOR-AVON

www.avon.com

MADE IN KOREA
DISTR. THE AVON COMPANY,
NEW YORK, NY 10006
©2023 THE AVON COMPANY

PRINCIPAL DISPLAY PANEL

ISA KNOX

ANEW

SOLAIRE

50
SPF

EVERYDAY
MINERAL FACE

PROTECTION CREAM
BROAD SPECTRUM SPF 50 SUNSCREEN

WATER-RESISTANT (40 MINUTES)

50 ml/1.7 fl.oz. U.S.